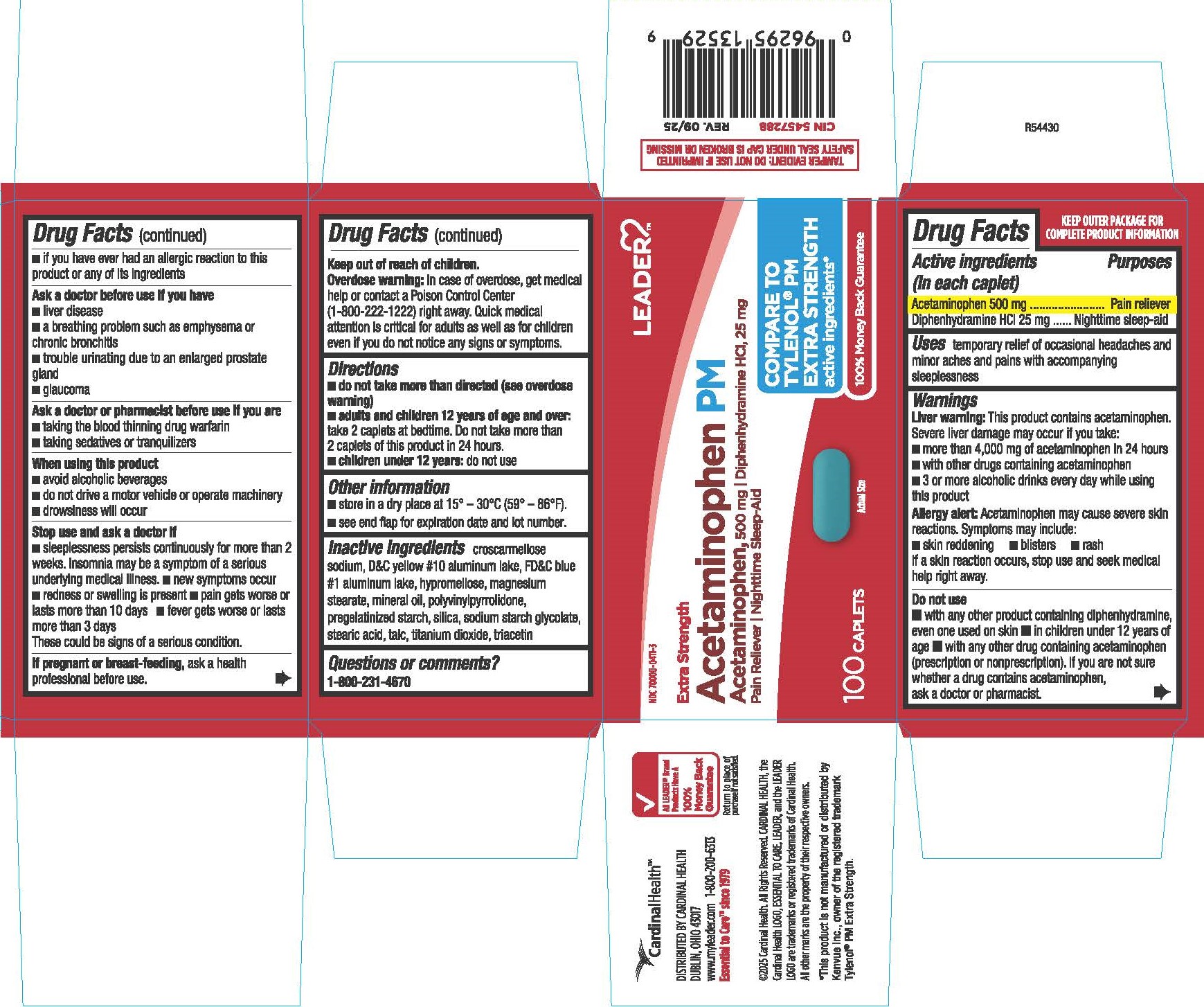 DRUG LABEL: Acetaminophen, Diphenhydramine Hydrochloride
NDC: 70000-0411 | Form: TABLET, FILM COATED
Manufacturer: LEADER/ Cardinal Health 110, Inc.
Category: otc | Type: HUMAN OTC DRUG LABEL
Date: 20260226

ACTIVE INGREDIENTS: ACETAMINOPHEN 500 mg/1 1; DIPHENHYDRAMINE HYDROCHLORIDE 25 mg/1 1
INACTIVE INGREDIENTS: TALC; TITANIUM DIOXIDE; STEARIC ACID; LIGHT MINERAL OIL; D&C YELLOW NO. 10; MAGNESIUM STEARATE; TRIACETIN; FD&C BLUE NO. 1; CROSCARMELLOSE SODIUM; POVIDONE K30; STARCH, CORN; SILICON DIOXIDE; HYPROMELLOSES; SODIUM STARCH GLYCOLATE TYPE A POTATO

0752-Cardinal

Drug Facts

Active ingredients (in each caplet)

Acetaminophen 500 mg

Diphenhydramine HCl 25 mg

Purposes

Pain reliever

Nighttime sleep-aid

Uses

temporary relief of occasional headaches and minor aches and pains with accompanying sleeplessness

WARNINGS

Liver warning:This product contains acetaminophen. Severe liver damage may occur if you take:

■ more than 4,000 mg of acetaminophen in 24 hours

■ with other drugs containing acetaminophen

■ 3 or more alcoholic drinks every day while using this product

Allergy alert: Acetaminophen may cause severe skin reactions. Symptoms may include: ■ skin reddening ■ blisters ■ rash

If a skin reaction occurs, stop use and seek medical help right away.

Do not use

- with any other product containing diphenhydramine, even one used on skin
- in children under 12 years of age
- with any other drug containing acetaminophen (prescription or nonprescription). If you are not sure whether a drug contains acetaminophen, ask a doctor or pharmacist.
- if you have ever had an allergic reaction to this product or any of its ingredients

Ask a doctor before use if you have

- liver disease
- a breathing problem such as emphysema or chronic bronchitis
- trouble urinating due to an enlarged prostate gland
- glaucoma

Ask a doctor or pharmacist before use if you are

- taking the blood thinning drug warfarin
- taking sedatives or tranquilizers

When using this product

- avoid alcoholic beverages
- do not drive a motor vehicle or operate machinery
- drowsiness will occur

Stop use and ask a doctor if

- sleeplessness persists continuously for more than 2 weeks. Insomnia may be a symptom of a serious underlying medical illness.
- new symptoms occur
- redness or swelling is present
- pain gets worse or lasts more than 10 days
- fever gets worse or lasts more than 3 days

These could be signs of a serious condition.

PREGNANCY OR BREAST FEEDING

If pregnant or breast-feeding, ask a health professional before use.

Keep out of reach of children.

OVERDOSAGE

Overdose warning: In case of overdose, get medical help or contact a Poison Control Center (1-800-222-1222) right away. Quick medical attention is critical for adults as well as for children even if you do not notice any signs or symptoms.

Directions

- do not take more than directed (see overdose warning)
- adults and children 12 years of age and over: take 2 caplets at bedtime. Do not take more than 2 caplets of this product in 24 hours.
- children under 12 years: do not use

Other information

- store in a dry place at 15°-30°C (59°-86°F).
- see end flap for expiration date and lot number.

INACTIVE INGREDIENT

croscarmellose sodium, D&C yellow #10 aluminum lake, FD&C blue #1 aluminum lake, hypromellose, magnesium stearate, mineral oil, polyvinylpyrrolidone, pregelatinized starch, silica, sodium starch glycolate, stearic acid, talc, titanium dioxide, triacetin

Questions or comments?

1-800-231-4670

*This product is not manufactured or distributed by Kenvue Inc., owner of the registered trademark Tylenol® PM Extra Strength.

TAMPER EVIDENT: DO NOT USE IF IMPRINTED SAFETY SEAL UNDER CAP IS BROKEN OR MISSING

DISTRIBUTED BY CARDINAL HEALTH

DUBLIN, OHIO 43017

www.myleader.com 1-800-200-6313

© 2025 Cardinal Health. All Rights Reserved. CARDINAL HEALTH, the Cardinal Health LOGO, ESSENTIAL TO CARE, LEADER, and the LEADER LOGO are trademarks or registered trademarks of Cardinal Health. All other marks are the property of their respective owners.

100% Money Back Guarantee

Return to place of purchase if not satisfied

PACKAGE LABEL

LEADERTM

NDC 70000-0411-3

Extra Strength Acetaminophen PM

Acetaminophen, 500 mg

Diphenhydramine HCl, 25 mg

Pain Reliever/Nighttime Sleep-Aid

COMPARE TO TYLENOL® PM EXTRA STRENGTH active ingredients*

100 CAPLETS